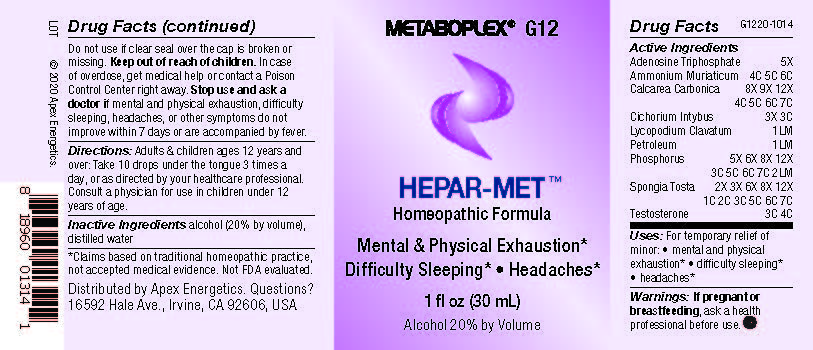 DRUG LABEL: G12
NDC: 63479-0712 | Form: SOLUTION/ DROPS
Manufacturer: Apex Energetics Inc.
Category: homeopathic | Type: HUMAN OTC DRUG LABEL
Date: 20240108
DEA Schedule: CIII

ACTIVE INGREDIENTS: ADENOSINE TRIPHOSPHATE 5 [hp_X]/1 mL; CHICORY ROOT 3 [hp_C]/1 mL; LYCOPODIUM CLAVATUM SPORE 1 [hp_Q]/1 mL; PHOSPHORUS 2 [hp_Q]/1 mL; SPONGIA OFFICINALIS SKELETON, ROASTED 7 [hp_C]/1 mL; KEROSENE 1 [hp_Q]/1 mL; OYSTER SHELL CALCIUM CARBONATE, CRUDE 7 [hp_C]/1 mL; AMMONIUM CHLORIDE 6 [hp_C]/1 mL; TESTOSTERONE 4 [hp_C]/1 mL
INACTIVE INGREDIENTS: ALCOHOL; WATER

G12

Active Ingredients
Adenosine Triphosphate | 5X
Ammonium Muriaticum | 4C 5C 6C
Calcarea Carbonica | 8X 9X 12X 4C 5C 6C 7C
Cichorium Intybus | 3X 3C
Lycopodium Clavatum | 1LM
Petroleum | 1LM
Phosphorus | 5X 6X 8X 12X 3C 5C 6C 7C 2LM
Spongia Tosta | 2X 3X 6X 8X 12X 1C 2C 3C 5C 6C 7C
Testosterone | 3C 4C

INDICATIONS AND USAGE

Uses:

For temporary relief of minor:

mental and physical exhaustion*

difficulty sleeping*

headaches*

*Claims based on traditional homeopathic practice, not accepted medical evidence. Not FDA evaluated.

Warnings:

PREGNANCY OR BREAST FEEDING

If pregnant or breastfeeding, ask a health professional before use.

Do not use if clear seal over the cap is broken or missing.

Keep out of reach of children. In case of overdose, get medical help or contact a Poison Control Center right away.

Stop use and ask a doctor if mental and physical exhaustion, difficulty sleeping, headaches, or other symptoms do not improve within 7 days or are accompanied by fever.

Directions:

Adults & children ages 12 years and over: Take 10 drops under the tongue 3 times a day, or as directed by your healthcare professional. Consult a physician for use in children under 12 years of age.

Inactive Ingredients

alcohol (20% by volume), distilled water

Distributed by Apex Energetics. Questions?

16592 Hale Ave., Irvine, CA 92606, USA

PACKAGE LABEL

METABOPLEX® G12

HEPAR-MET™

Homeopathic Formula

Mental & Physical Exhaustion*

Difficulty Sleeping* • Headaches*

1 fl oz (30 mL)

Alcohol 20% by Volume